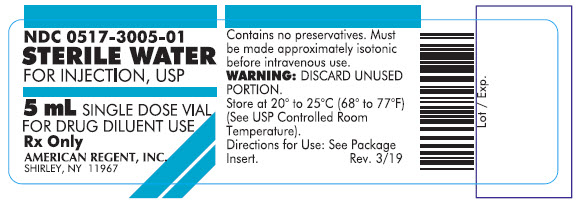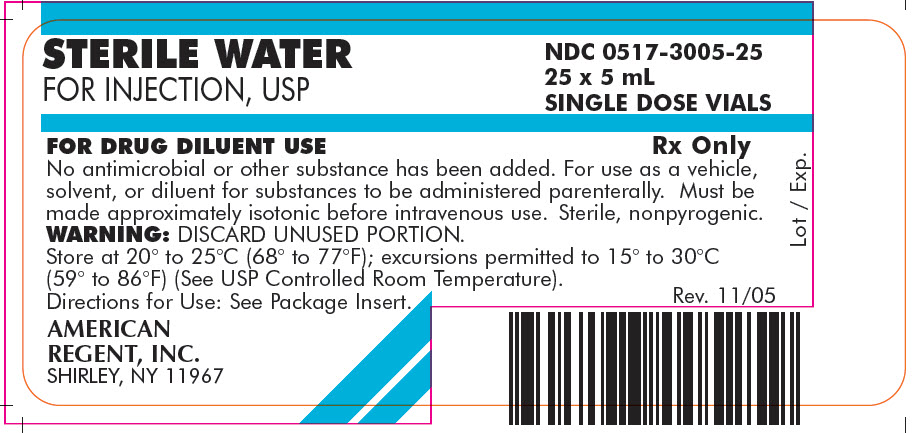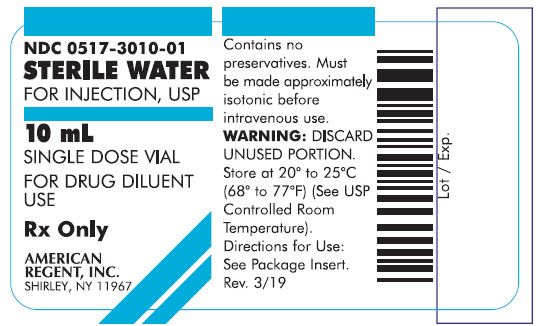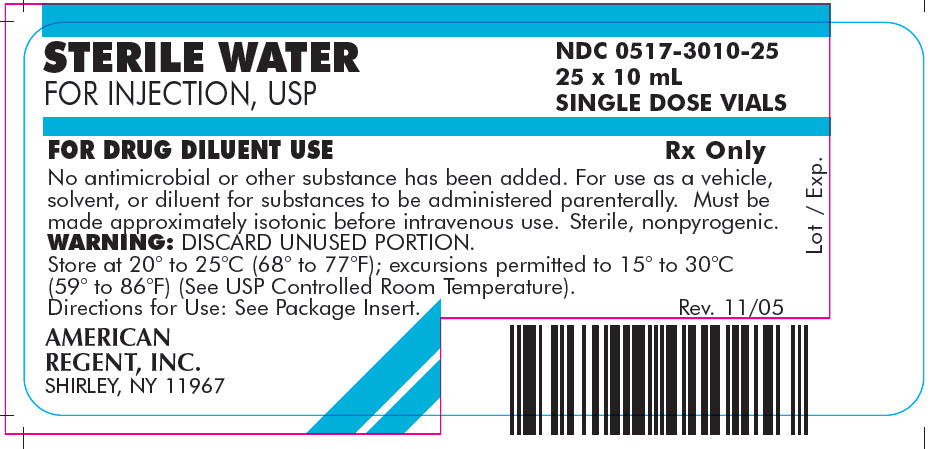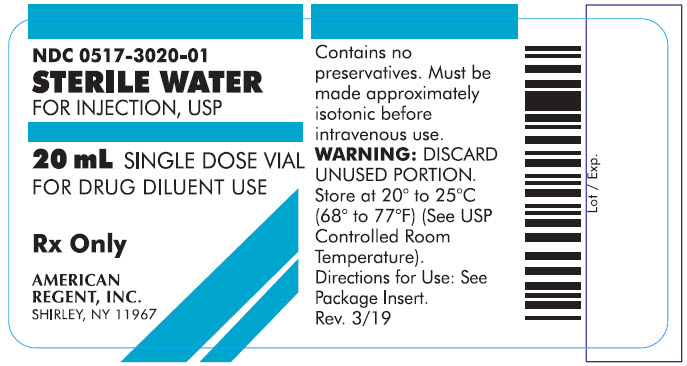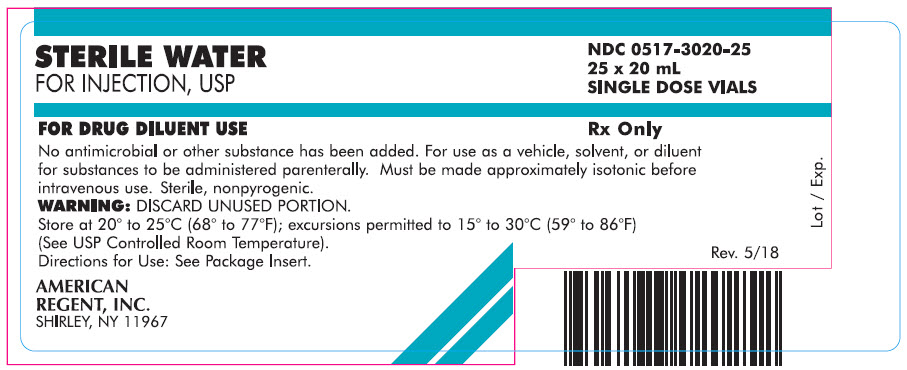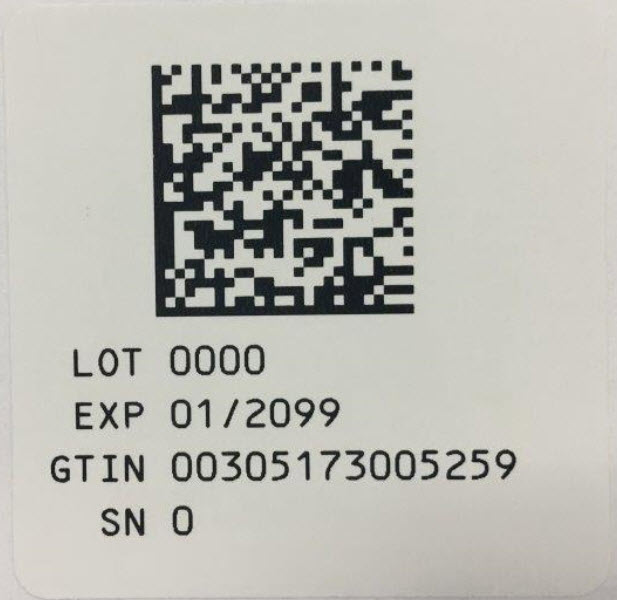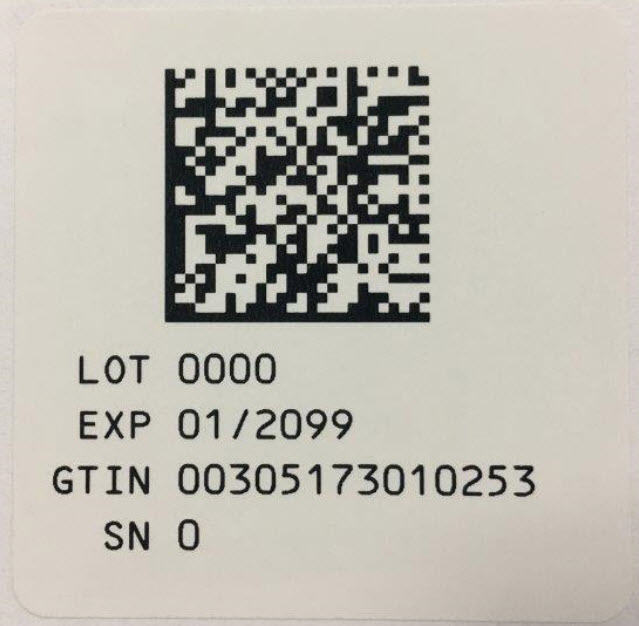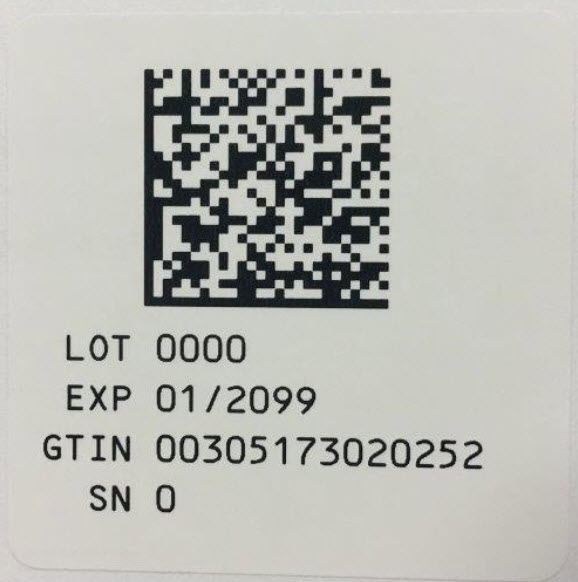 DRUG LABEL: Sterile Water
NDC: 0517-3005 | Form: INJECTION, SOLUTION
Manufacturer: American Regent, Inc.
Category: prescription | Type: HUMAN PRESCRIPTION DRUG LABEL
Date: 20220131

ACTIVE INGREDIENTS: WATER 1 mL/1 mL

STERILE WATER FOR INJECTION, USP
(pH 5.0-7.0)

Rx Only

BOXED WARNING

NOT FOR DIRECT INJECTION

DESCRIPTION:

Sterile Water for Injection, USP is water for injection sterilized and packaged in single dose vials. It contains no antimicrobial agents or other preservatives. It is used as a diluent. Non-pyrogenic.

PRECAUTIONS:

Unused amount should be discarded immediately following withdrawal of any portion of vial contents. Sterile Water for Injection is not isotonic and should not be injected directly into the body.

Store at 20° to 25°C (68° to 77°F); excursions permitted to 15° to 30°C (59° to 86°F) (See USP Controlled Room Temperature).

Parenteral drug products should be inspected visually for particulate matter and discoloration, whenever solution and container permit.

HOW SUPPLIED:

Sterile Water for Injection, USP

NDC 0517-3005-25 | 5 mL Single Dose Vial | Packaged in 25
NDC 0517-3010-25 | 10 mL Single Dose Vial | Packaged in 25
NDC 0517-3020-25 | 20 mL Single Dose Vial | Packaged in 25
NDC 0517-3050-25 | 50 mL Single Dose Vial | Packaged in 25

AMERICAN
REGENT, INC.
SHIRLEY, NY 11967

IN3005
Rev. 1/09

PRINCIPAL DISPLAY PANEL - 5 mL

Contain

NDC 0517-3005-01

STERILE WATER
FOR INJECTION, USP

5 mL SINGLE DOSE VIAL

FOR DRUG DILUENT USE

Rx Only

AMERICAN REGENT, INC.
SHIRLEY, NY 11967
Carton
STERILE WATER
FOR INJECTION, USP
NDC 0517-3005-25
25 x 5 mL
SINGLE DOSE VIALS

FOR DRUG DILUENT USE

Rx Only
No antimicrobial or other substance has been added. For use as a vehicle, solvent, or diluent for substances to be administered parenterally. Must be made approximately isotonic before intravenous use. Sterile, nonpyrogenic.
WARNING: DISCARD UNUSED PORTION.
Store at 20° to 25°C (68° to 77°F); excursions permitted to 15° to 30°C (59° to 86°F) (See USP Controlled Room Temperature).
Directions for Use: See Package Insert.

AMERICAN
REGENT, INC.
SHIRLEY, NY 11967
Rev. 11/05

PRINCIPAL DISPLAY PANEL - 10 mL

Container

NDC 0517-3010-01

STERILE WATER
FOR INJECTION, USP

10 mL SINGLE DOSE VIAL

FOR DRUG DILUENT USE

Rx Only

AMERICAN REGENT, INC.
SHIRLEY, NY 11967
Carton
STERILE WATER
FOR INJECTION, USP
NDC 0517-3010-25
25 x 10 mL
SINGLE DOSE VIALS

FOR DRUG DILUENT USE

Rx Only
No antimicrobial or other substance has been added. For use as a vehicle, solvent, or diluent for substances to be administered parenterally. Must be made approximately isotonic before intravenous use. Sterile, nonpyrogenic.
WARNING: DISCARD UNUSED PORTION.
Store at 20° to 25°C (68° to 77°F); excursions permitted to 15° to 30°C (59° to 86°F) (See USP Controlled Room Temperature).
Directions for Use: See Package Insert.

AMERICAN
REGENT, INC.
SHIRLEY, NY 11967
Rev. 11/05

PRINCIPAL DISPLAY PANEL - 20 mL

Container

NDC 0517-3020-01

STERILE WATER
FOR INJECTION, USP

20 mL SINGLE DOSE VIAL

FOR DRUG DILUENT USE

Rx Only

AMERICAN REGENT, INC.
SHIRLEY, NY 11967

Carton
STERILE WATER
FOR INJECTION, USP
NDC 0517-3020-25
25 x 20 mL
SINGLE DOSE VIALS

FOR DRUG DILUENT USE

Rx Only
No antimicrobial or other substance has been added. For use as a vehicle, solvent, or diluent for substances to be administered parenterally. Must be made approximately isotonic before intravenous use. Sterile, nonpyrogenic.
WARNING: DISCARD UNUSED PORTION.
Store at 20° to 25°C (68° to 77°F); excursions permitted to 15° to 30°C (59° to 86°F) (See USP Controlled Room Temperature).
Directions for Use: See Package Insert.

AMERICAN
REGENT, INC.
SHIRLEY, NY 11967
Rev. 5/18